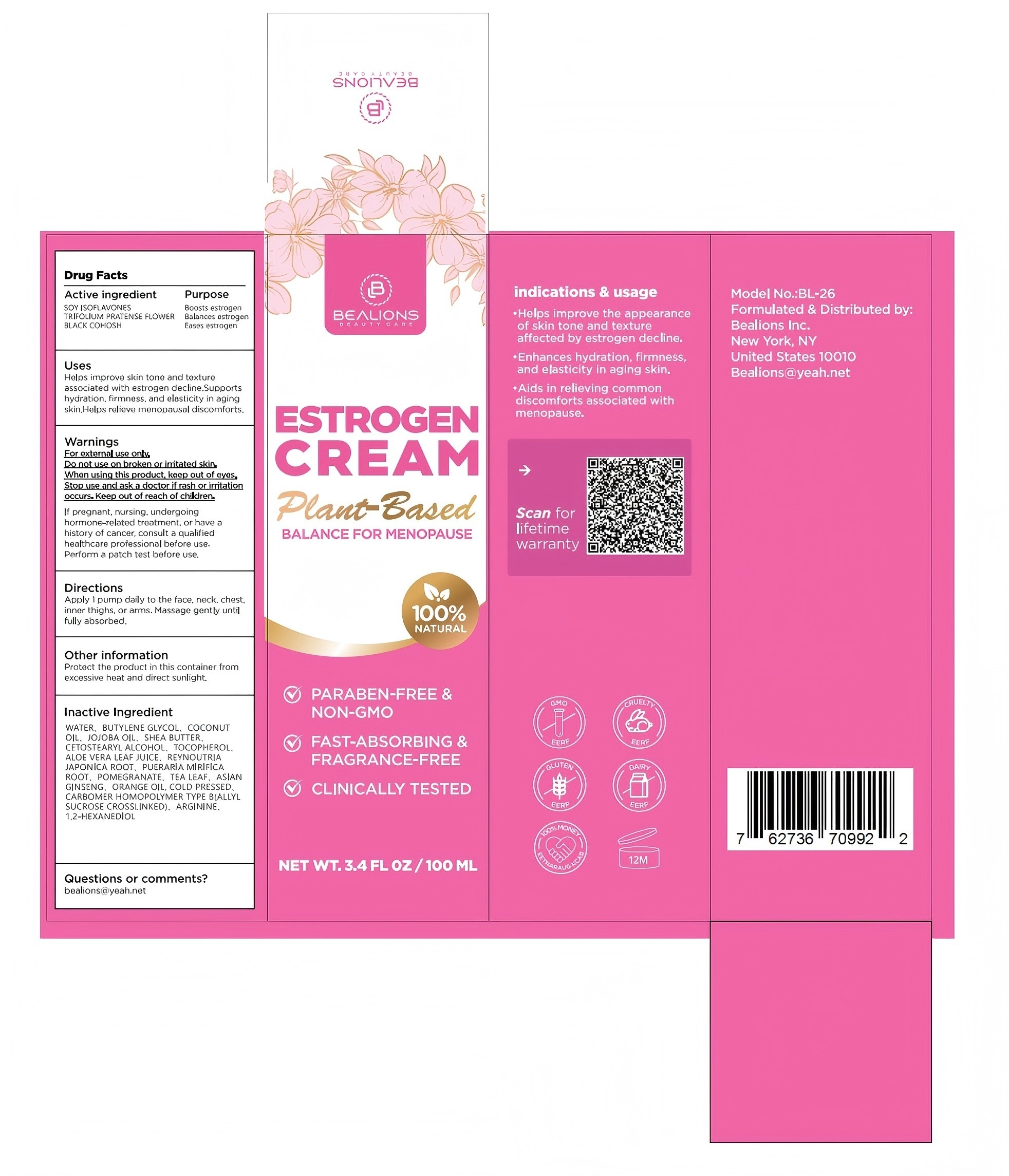 DRUG LABEL: Bealions Estrogen
NDC: 87336-001 | Form: CREAM
Manufacturer: Guangdong Yucheng Cosmetics Co., Ltd
Category: otc | Type: HUMAN OTC DRUG LABEL
Date: 20260113

ACTIVE INGREDIENTS: TRIFOLIUM PRATENSE FLOWER 0.5 g/100 mL; SOY ISOFLAVONES 1.2 g/100 mL; BLACK COHOSH 0.5 g/100 mL
INACTIVE INGREDIENTS: ASIAN GINSENG; 1,2-HEXANEDIOL; SHEA BUTTER; PUERARIA MIRIFICA ROOT; JOJOBA OIL; POMEGRANATE; TEA LEAF; ARGININE; BUTYLENE GLYCOL; TOCOPHEROL; COCONUT OIL; REYNOUTRIA JAPONICA ROOT; WATER; ALOE VERA LEAF JUICE; ORANGE OIL, COLD PRESSED; CETOSTEARYL ALCOHOL; CARBOMER HOMOPOLYMER TYPE B (ALLYL PENTAERYTHRITOL CROSSLINKED)

INACTIVE INGREDIENT

WATER
BUTYLENE GLYCOL
COCONUT OIL
JOJOBA OIL
SHEA BUTTER
CETOSTEARYL ALCOHOL
TOCOPHEROL
ALOE VERA LEAF JUICE
REYNOUTRIA JAPONICA ROOT
PUERARIA MIRIFICA ROOT
POMEGRANATE
TEA LEAF
ASIAN GINSENG
ORANGE OIL, COLD PRESSED
CARBOMER HOMOPOLYMER TYPE B
(ALLYL SUCROSE CROSSLINKED)
ARGININE
1,2-HEXANEDIOL

DOSAGE AND ADMINISTRATION

Apply 1 pump daily to the face, neck, chest,inner thighs, or arms. Massage gently until fully absorbed.

WARNINGS

For ecternal use only.

ACTIVE INGREDIENT

SOY ISOFLAVONES 1.2％
BLACK COHOSH 0.5％
TRIFOLIUM PRATENSE FLOWER 0.5％

KEEP OUT OF REACH OF CHILDREN

Keep out of eyes: In case of contact with eyes, please fush thoroughly with water.

INDICATIONS AND USAGE

Uses：Helps improve skin tone and texture associated with estrogen decline.Supports hydration, firmness, and elasticity in aging
skin.Helps relieve menopausal discomforts.

PURPOSE

Boosts estrogen
Balances estrogen
Eases estrogen